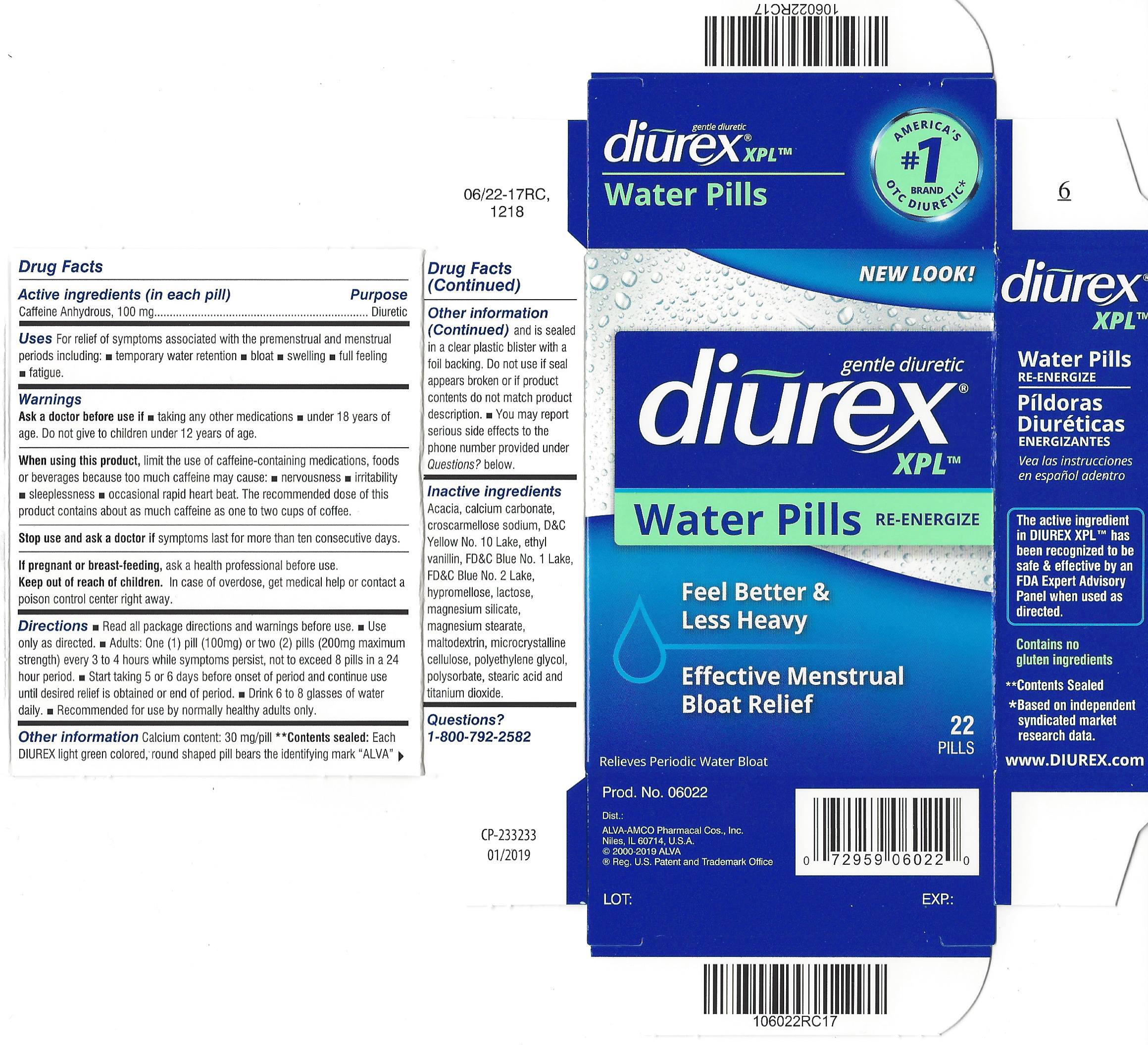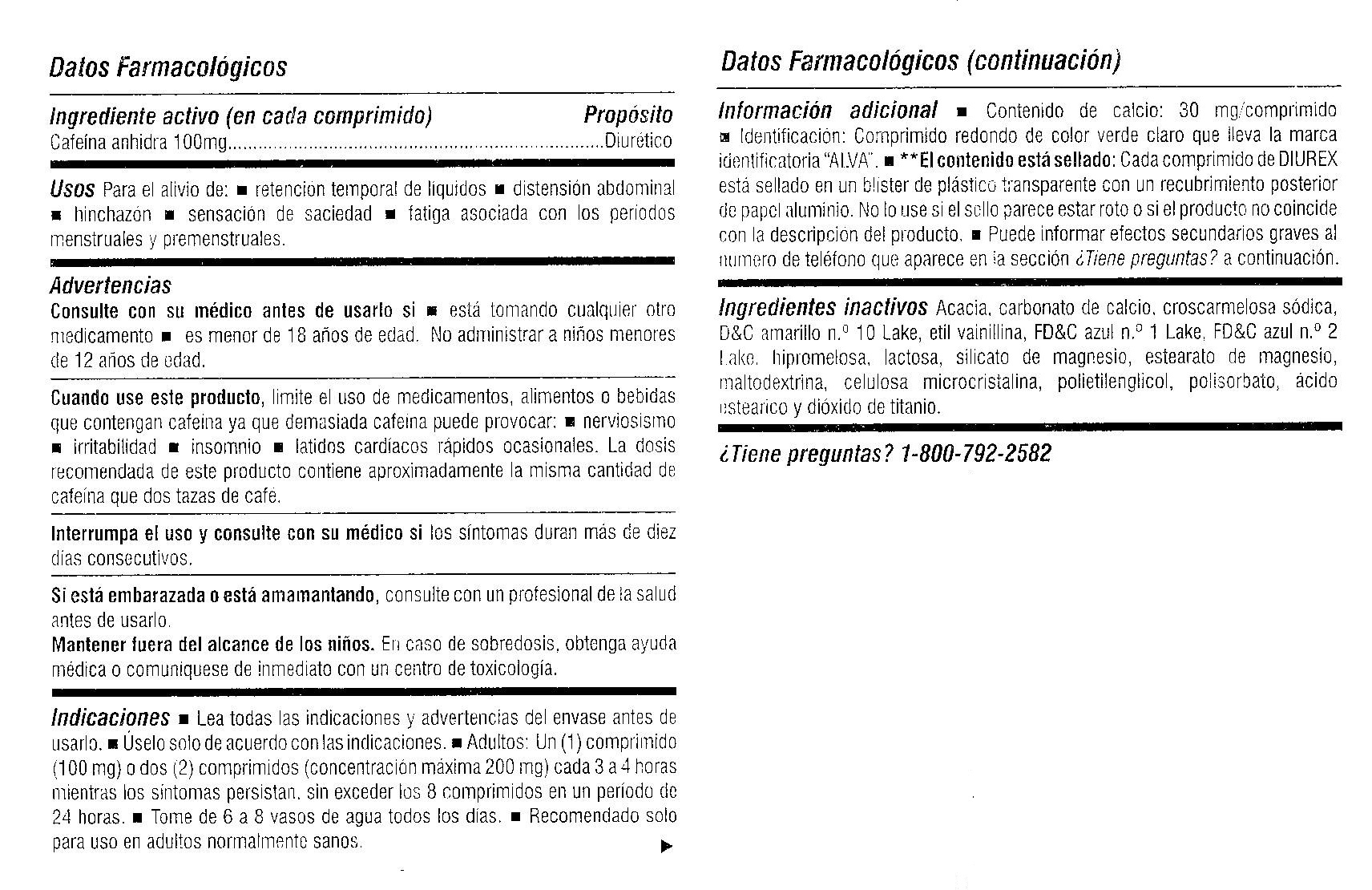 DRUG LABEL: Diurex Water Pills
NDC: 52389-406 | Form: TABLET, FILM COATED
Manufacturer: Kobayashi Healthcare International, Inc.
Category: otc | Type: HUMAN OTC DRUG LABEL
Date: 20251021

ACTIVE INGREDIENTS: CAFFEINE 100 mg/1 1
INACTIVE INGREDIENTS: CALCIUM CARBONATE; CROSCARMELLOSE SODIUM; ETHYL VANILLIN; D&C YELLOW NO. 10; FD&C BLUE NO. 1; FD&C BLUE NO. 2; ACACIA; HYPROMELLOSES; TALC; MAGNESIUM STEARATE; MALTODEXTRIN; CELLULOSE, MICROCRYSTALLINE; POLYETHYLENE GLYCOL 400; POLYSORBATE 80; STEARIC ACID; TITANIUM DIOXIDE; LACTOSE MONOHYDRATE

Diurex XPL

Active ingredient (in each pill)

Caffeine Anhydrous, 100 mg

Purpose

Diuretic

Uses

For relief of symptoms associated with the premenstrual and menstrual periods including:

- temporary water retention
- bloat
- swelling
- full feeling
- fatigue

Ask a doctor before use if

- taking any other medications
- under 18 years of age. Do not give to children under 12 years of age.

When using this product, limit the use of caffeine-containing medications, foods or beverages because too much caffeine may cause:

- nervousness
- irritability
- sleeplessness
- occasional rapid heart beat. The recommended dose of this product contains about as much caffeine as one to two cups of coffee.

Stop use and ask a doctor if symptoms last for more than ten consecutive days.

PREGNANCY OR BREAST FEEDING

If pregnant or breastfeeding, ask a health professional before use.

Keep out of reach of children. In case of overdose, get medical help or contact a poison control center right away.

Directions

- Read all package directions and warnings before use.
- Use only as directed.
- Adults: One (1) pill (100mg) or two (2) pills (200 mg maximum strength) every 3 to 4 hours while symptoms persist, not to exceed 8 pills in a 24 hour period.
- Start taking 5 or 6 days before onset of period and continue use until desired relief is obtained or end of period.
- Drink 6 to 8 glasses of water daily.
- Recommended for use by normally healthy adults only.

Other information

- Calcium content: 30 mg/pill
- **Contents sealed: Each DIUREX light green colored, round shaped pill bears the identifying mark "ALVA" and is sealed in a clear plastic blister with a foil backing. Do not use if seal appears broken or if product contents do not match product description.
- You may report serious side effects to the phone number provided under Questions? below.

Inactive ingredients

Acacia, calcium carbonate, croscarmellose sodium, D&C Yellow No. 10 Lake, ethyl vanillin, FD&C Blue No. 1 Lake, FD&C Blue No. 2 Lake, hypromellose, lactose, magnesium silicate, magnesium stearate, maltodextrin, microcrystalline cellulose, polyethylene glycol, polysorbate, stearic acid and titanium dioxide.

Questions? 1-800-792-2582